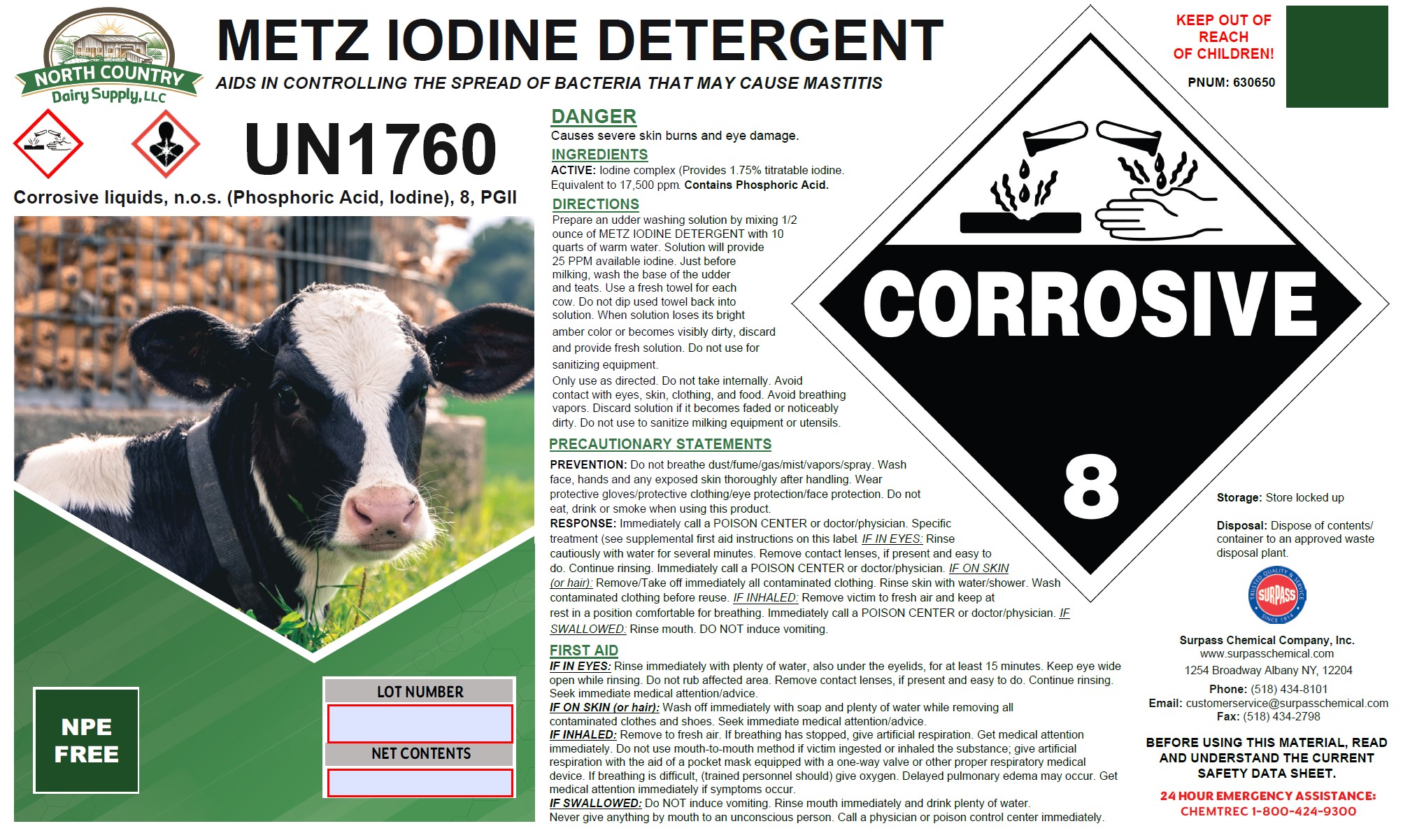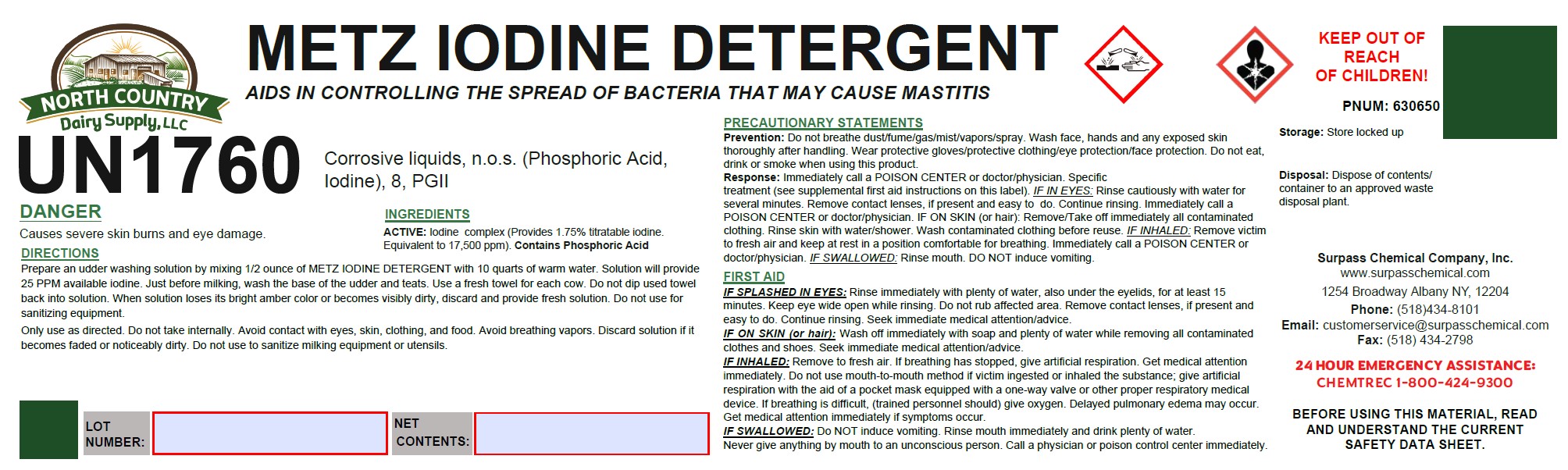 DRUG LABEL: Metz Iodine Detergent
NDC: 86067-0123 | Form: SOLUTION
Manufacturer: Surpass Chemical. Company, Inc.
Category: animal | Type: OTC ANIMAL DRUG LABEL
Date: 20240506

ACTIVE INGREDIENTS: IODINE 0.0875 kg/1 kg
INACTIVE INGREDIENTS: WATER 0.7192 kg/1 kg; C9-11 PARETH-8 0.1066 kg/1 kg; PHOSPHORIC ACID 0.0867 kg/1 kg

Metz Iodine Detergent

DESCRIPTION

METZ IODINE DETERGENT

AIDS IN CONTROLLING THE SPREAD OF BACTERIA THAT MAY CAUSE MASTITIS PRODUCT #: 630650

USER SAFETY WARNINGS

DANGER

Causes severe skin burns and eye damage.

DIRECTIONS:
Prepare an udder washing solution by mixing 1/2 ounce of METZ IODINE DETERGENT with 10 quarts of warm water.
Solution will provide 25 PPM available iodine. Just before milking, wash the base of the udder and teats. Use a fresh towel for each cow. Do not dip used towel back into solution. When solution loses its bright amber color or becomes visibly dirty, discard and provide fresh solution. Do not use for sanitizing equipment.

Only use as directed. Do not take internally. Avoid contact with eyes, skin, clothing, and food. Avoid breathing vapors. Discard solution if it becomes faded or noticeably dirty. Do not use to sanitize milking equipment or utensils.

ACTIVE INGREDIENT

INGREDIENTS:
ACTIVE: Iodine complex (Provides 1.75% titratable iodine. Equivalent to 17,500 ppm).

Contains Phosphoric Acid

OTHER SAFETY INFORMATION

FIRST AID:

IF SPLASHED IN EYES: Rinse immediately with plenty of water, also under the eyelids, for at least 15 minutes. Keep eye wide open while rinsing. Do not rub affected area. Remove contact lenses, if present and easy to do. Continue rinsing. Seek immediate medical attention/advice.
IF ON SKIN (or hair) Wash off immediately with soap and plenty of water while removing all contaminated clothes and shoes. Seek immediate medical attention/advice.
IF INHALED: Remove to fresh air. If breathing has stopped, give artificial respiration. Get medical attention immediately. Do not use mouth-to-mouth method if victim ingested or inhaled the substance; give artificial respiration with the aid of a pocket mask equipped with a one-way valve or other proper respiratory medical device. If breathing is difficult, (trained personnel should) give oxygen. Delayed pulmonary edema may occur. Get medical attention immediately if symptoms occur.
IF SWALLOWED: Do NOT induce vomiting. Rinse mouth immediately and drink plenty of water. Never give anything by mouth to an unconscious person. Call a physician or poison control center immediately.

PRECAUTIONS

PRECAUTIONARY STATEMENTS
Prevention: Do not breathe dust/fume/gas/mist/vapors/spray. Wash face, hands and any exposed skin thoroughly after handling. Wear protective gloves/protective clothing/eye protection/face protection. Do not eat, drink or smoke when using this product.
Response: Immediately call a POISON CENTER or doctor/physician. Specific treatment (see supplemental first aid instructions on this label)
IF IN EYES: Rinse cautiously with water for several minutes. Remove contact lenses, if present and easy to
do. Continue rinsing. Immediately call a POISON CENTER or doctor/physician. IF ON SKIN (or hair): Remove/Take off immediately all contaminated clothing. Rinse skin with water/shower. Wash contaminated clothing before reuse. IF INHALED: Remove victim to fresh air and keep at rest in a position comfortable for breathing. Immediately call a POISON CENTER or doctor/physician.
IF SWALLOWED: Rinse mouth. DO NOT induce vomiting.

Storage Disposal

Store locked up. Dispose of contents/container to an approved waste disposal plant.

KEEP OUT OF REACH OF CHILDREN!

Surpass Chemical Company, Inc. Phone: (518) 434-8101 24 HOUR EMERGENCY ASSISTANCE

www.surpasschemical.com Fax: (518) 434-2798 CHEMTREC 1-800-424-9300
1254 Broadway Albany NY, 12204 Email: customerservice@surpasschemical.com